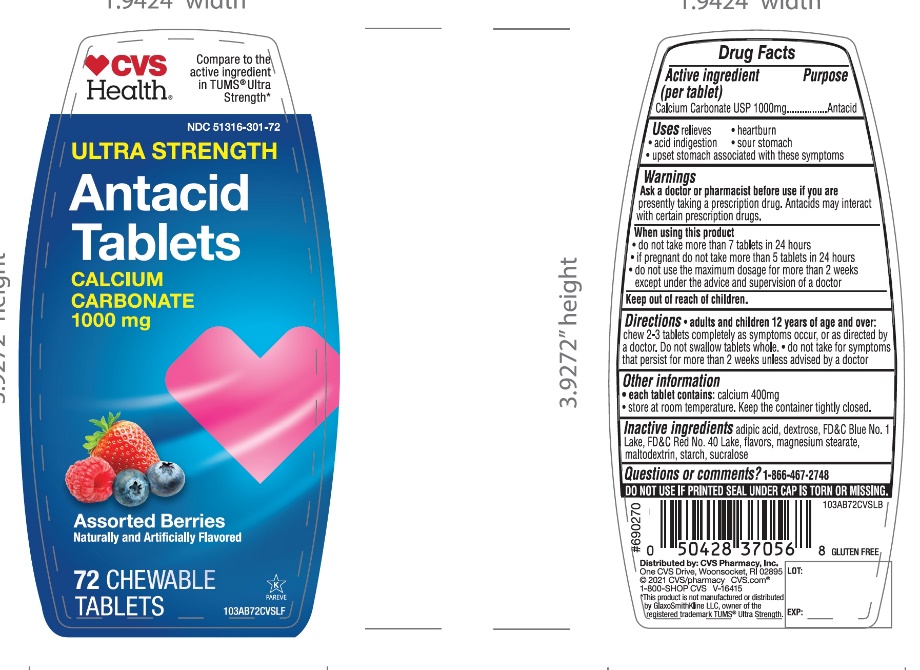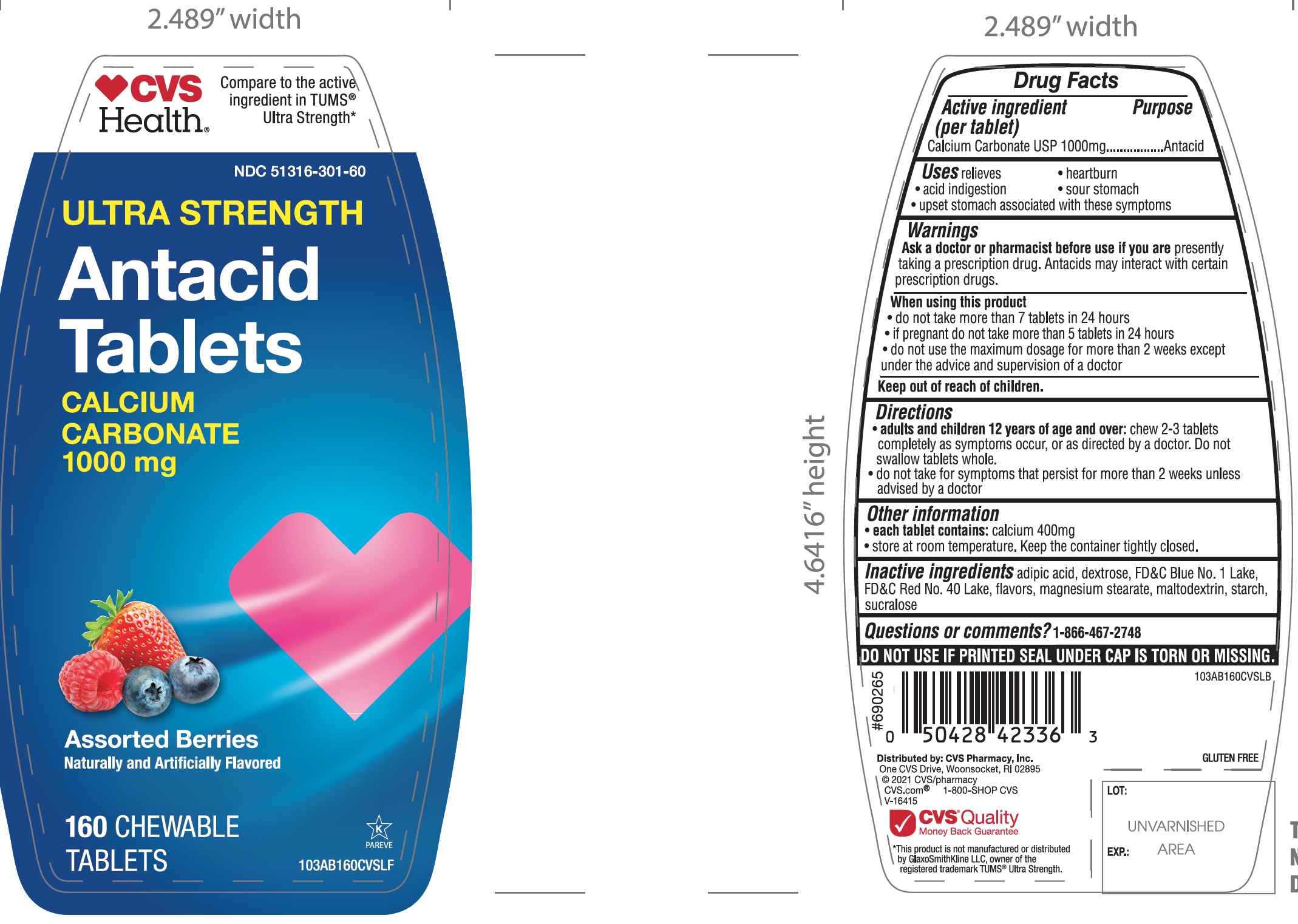 DRUG LABEL: CVS PHARMACY

NDC: 51316-301 | Form: TABLET, CHEWABLE
Manufacturer: CVS
Category: otc | Type: HUMAN OTC DRUG LABEL
Date: 20251204

ACTIVE INGREDIENTS: CALCIUM CARBONATE 1000 mg/1 1
INACTIVE INGREDIENTS: MAGNESIUM STEARATE; MALTODEXTRIN; STARCH, CORN; SUCRALOSE; ADIPIC ACID; DEXTROSE, UNSPECIFIED FORM; FD&C BLUE NO. 1; FD&C RED NO. 40

CVS Ultra Strength Antacid 72 Chewable Tablets Drug Facts

Active ingredient (per tablet)

Calcium Carbonate USP 1000 mg

Purpose

Antacid

Uses

relieves

- heartburn
- acid indigestion
- sour stomach
- upset stomach associated with these symptoms

Ask a doctor or pharmacist before use if you are

presently taking a prescription drug. Antacids may interact with certain prescription drugs.

When using this product

- do not take more than 7 tablets in 24 hours
- if pregnant do not take more than 5 tablets in 24 hours
- do not use the maximum dosage for more than 2 weeks except under the advice and supervision of a doctor

Directions

- adults and children 12 years of age and over:chew 2-3 tablets completely as symptoms occur, or as directed by a doctor. Do not swallow tablets whole.
- do not take for symptoms that persist for more than 2 weeks unless advised by a doctor

Other information

- each tablet contains: calcium 400mg
- store at room temperature. Keep the container tightly closed.

Inactive ingredients

adipic acid, dextrose, FD&C Blue No. 1, FD&C Red No. 40, flavors, magnesium stearate, maltodextrin, starch, sucralose.

Questions or comments?

1-866-467-2748

Safety Sealed

DO NOT USE IF PRINTED SEAL UNDER CAP IS TORN OR MISSING

Package/Label Principal Display Panel

NDC# 51316-301-72

*Compare to the active ingredient in Ultra Strength Tums®

ULTRA STRENGTH

Antacid Tablets

Calcium Carbonate 1000 mg

Fast Relief of Upset Stomach, Heartburn, and Acid Indigestion

Assorted Berry

Naturally and Artificially Flavored

K PAREVE

GLUTEN FREE

72 Chewable Tablets

DISTRIBUTED

*This product is not manufactured or distributed by GlaxoSmithKline LLC, owner of the registered trademark, Ultra Strength Tums®

Package Label for 72 Chewable tablets